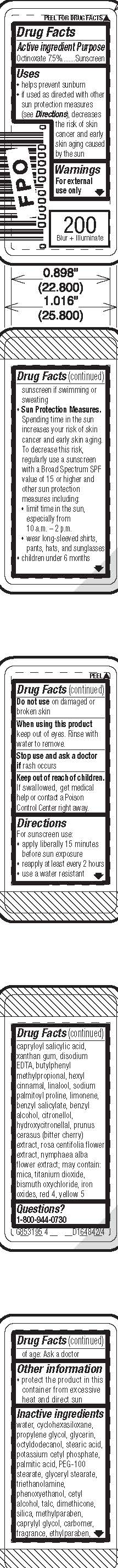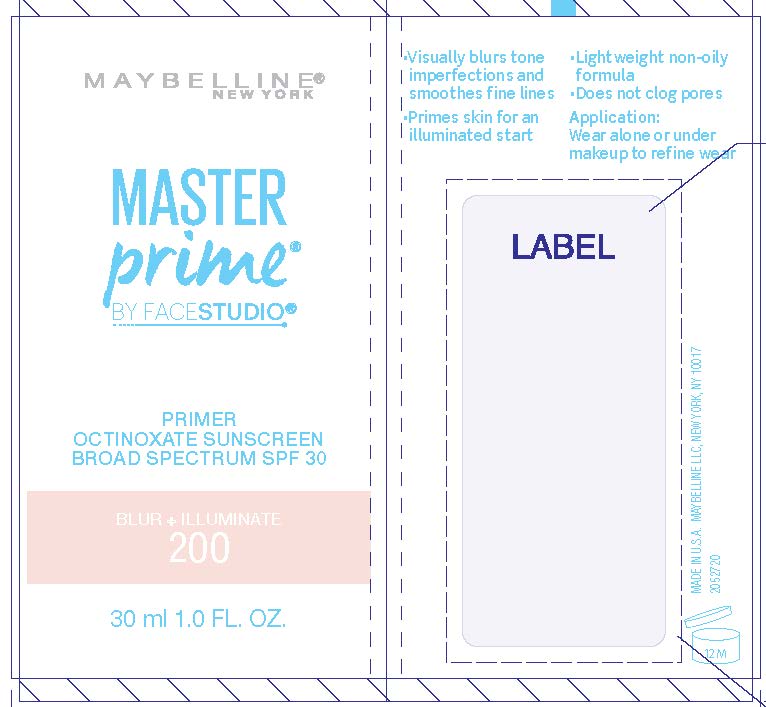 DRUG LABEL: Maybelline New York Master Prime By Face Studio Primer Broad Spectrum SPF 30 Sunscreen
NDC: 49967-196 | Form: LOTION
Manufacturer: L’Oreal USA Products Inc
Category: otc | Type: HUMAN OTC DRUG LABEL
Date: 20231228

ACTIVE INGREDIENTS: OCTINOXATE 75 mg/1 mL
INACTIVE INGREDIENTS: WATER; CYCLOMETHICONE 6; PROPYLENE GLYCOL; GLYCERIN; OCTYLDODECANOL; STEARIC ACID; POTASSIUM CETYL PHOSPHATE; PALMITIC ACID; PEG-100 STEARATE; GLYCERYL STEARATE SE; TROLAMINE; PHENOXYETHANOL; CETYL ALCOHOL; TALC; DIMETHICONE; SILICON DIOXIDE; METHYLPARABEN; CAPRYLYL GLYCOL; CARBOXYPOLYMETHYLENE; ETHYLPARABEN; CAPRYLOYL SALICYLIC ACID; XANTHAN GUM; EDETATE DISODIUM ANHYDROUS; BUTYLPHENYL METHYLPROPIONAL; .ALPHA.-HEXYLCINNAMALDEHYDE; LINALOOL, (+/-)-; SODIUM PALMITOYL PROLINE; LIMONENE, (+/-)-; BENZYL SALICYLATE; BENZYL ALCOHOL; .BETA.-CITRONELLOL, (R)-; HYDROXYCITRONELLAL; PRUNUS CERASUS FLOWER BUD; ROSA CENTIFOLIA FLOWER; NYMPHAEA ALBA FLOWER; MICA; TITANIUM DIOXIDE; BISMUTH OXYCHLORIDE; FERRIC OXIDE RED; FD&C RED NO. 4; FD&C YELLOW NO. 5

Drug Facts

Active ingredient

Octinoxate 7.5%

Purpose

Sunscreen

Uses

- helps prevent sunburn
- if used as directed with other sun protection measures (see Directions), decreases the risk of skin cancer and early skin aging caused by the sun

Warnings

For external use only

Do not use

on damaged or broken skin

When using this product

keep out of eyes. Rinse with water to remove.

Stop use and ask a doctor if

rash occurs

Keep out of reach of children.

If swallowed, get medical help or contact a Poison Control Center right away.

Directions

For sunscreen use:
● shake well

● apply liberally 15 minutes before sun exposure
● reapply at least every 2 hours
● use a water resistant sunscreen if swimming or sweating
● Sun Protection Measures. Spending time in the sun increases your risk of skin cancer and early skin aging. To decrease this risk, regularly use a sunscreen with a Broad Spectrum SPF value of 15 or higher and other sun protection measures including:
● limit time in the sun, especially from 10 a.m. – 2 p.m.
● wear long-sleeved shirts, pants, hats, and sunglasses
● children under 6 months of age: Ask a doctor

Other information

protect the product in this container from excessive heat and direct sun

Inactive ingredients

water, cyclohexasiloxane, propylene glycol, glycerin, octyldodecanol, stearic acid, potassium cetyl phosphate, palmitic acid, PEG-100 stearate, glyceryl stearate, triethanolamine, phenoxyethanol, cetyl alcohol, talc, dimethicone, silica, methylparaben, caprylyl glycol, carbomer, fragrance, ethylparaben, capryloyl salicylic acid, xanthan gum, disodium EDTA, butylphenyl methylpropional, hexyl cinnamal, linalool, sodium palmitoyl proline, limonene, benzyl salicylate, benzyl alcohol, citronellol, hydroxycitronellal, prunus cerasus (bitter cherry) extract, rosa centifolia flower extract, nymphaea alba flower extract; may contain: mica, titanium dioxide, bismuth oxychloride, iron oxides, red 4, yellow 5

Questions or comments?

1-800-944-0730